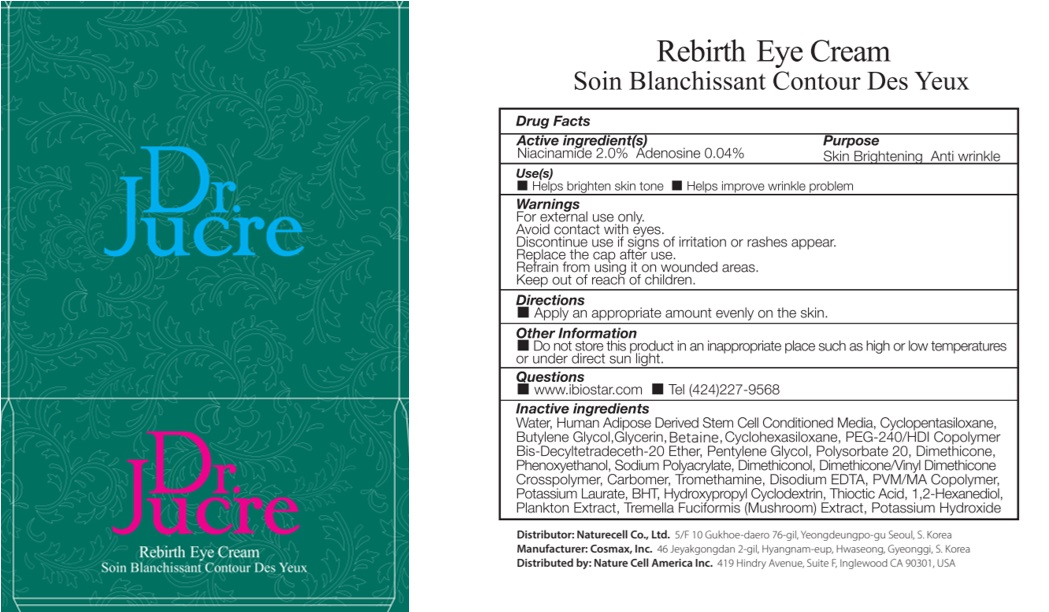 DRUG LABEL: Dr.Jucre Rebirth Eye
NDC: 83071-120 | Form: CREAM
Manufacturer: NATURECELL CO., LTD.
Category: otc | Type: HUMAN OTC DRUG LABEL
Date: 20250102

ACTIVE INGREDIENTS: NIACINAMIDE 2 g/100 mL; ADENOSINE 0.04 g/100 mL
INACTIVE INGREDIENTS: WATER; CYCLOMETHICONE 5; BUTYLENE GLYCOL

ACTIVE INGREDIENTS

Niacinamide 2.0%
Adenosine 0.04%

INACTIVE INGREDIENTS

Water, Human Adipose Derived Stem Cell Conditioned Media, Cyclopentasiloxane, Butylene Glycol, Glycerin, Cyclohexasiloxane, PEG-240/HDI Copolymer Bis-Decyltetradeceth-20 Ether, Pentylene Glycol, Polysorbate 20, Dimethicone, Phenoxyethanol, Sodium Polyacrylate, Dimethiconol, Dimethicone/Vinyl Dimethicone Crosspolymer, Carbomer, Tromethamine, Disodium EDTA, PVM/MA Copolymer, Potassium Laurate, BHT, Hydroxypropyl Cyclodextrin, Thioctic Acid, 1,2-Hexanediol, Plankton Extract, Tremella Fuciformis (Mushroom) Extract, Potassium Hydroxide

PURPOSE

Skin Brightening
Anti wrinkle

WARNINGS

For external use only.
Avoid contact with eyes.
Discontinue use if signs of irritation or rashes appear.
Replace the cap after use.
Refrain from using it on wounded areas.
Keep out of reach of children.

KEEP OUT OF REACH OF CHILDREN

Keep out of the reach of children.

Uses

■ Helps brighten skin tone
■ Helps improve wrinkle problem

Directions

■ Apply an appropriate amount evenly on the skin.

Other Information

■ Do not store this product in an inappropriate place such as high or low temperatures or under direct sun light.

Questions

■ www.ibiostar.com
■ Tel (424)227-9568